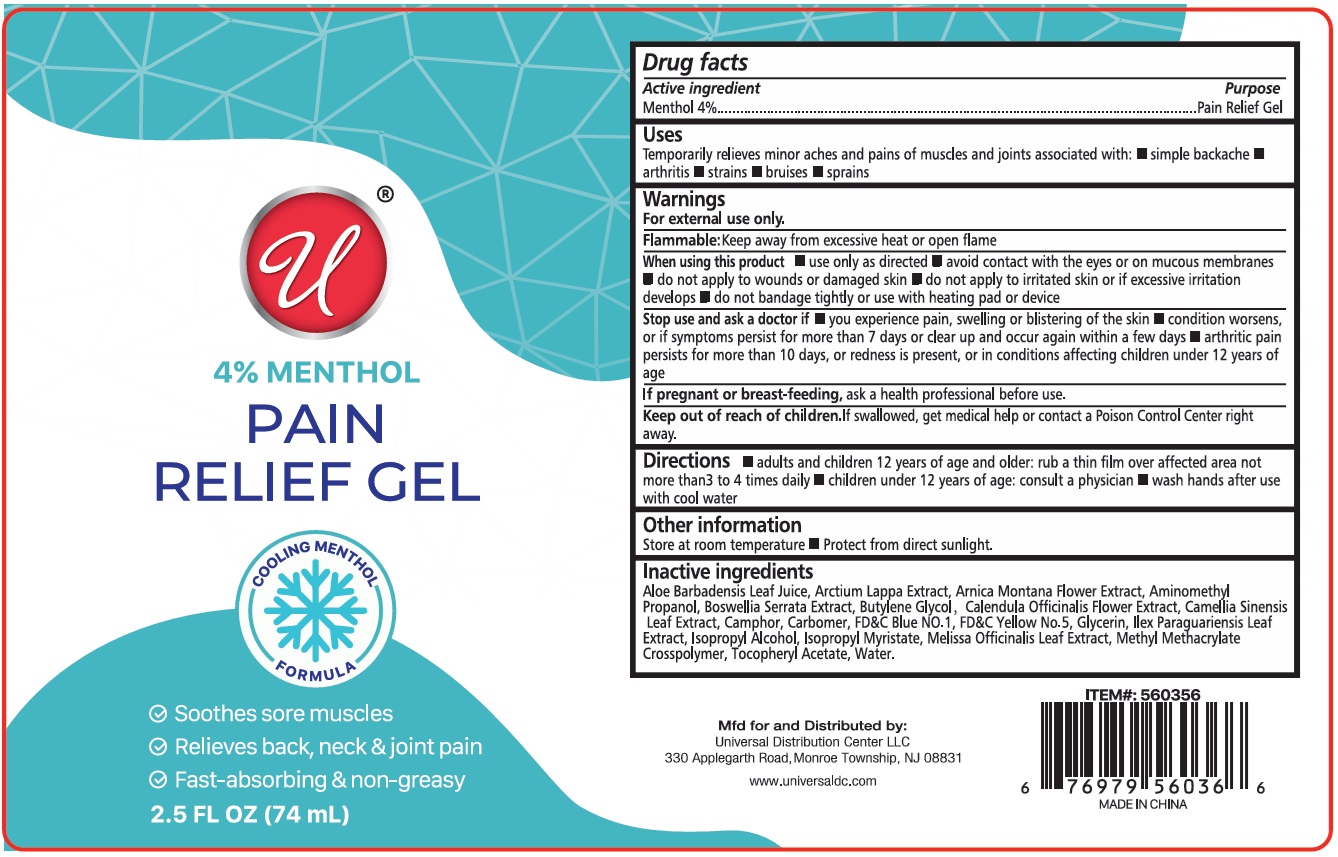 DRUG LABEL: 4% Menthol PAIN RELIEF
NDC: 43473-095 | Form: GEL
Manufacturer: Nantong Health & Beyond Hygienic Products Inc.
Category: otc | Type: HUMAN OTC DRUG LABEL
Date: 20260205

ACTIVE INGREDIENTS: MENTHOL, UNSPECIFIED FORM 4 g/100 mL
INACTIVE INGREDIENTS: ALOE VERA LEAF JUICE; ARCTIUM LAPPA WHOLE; ARNICA MONTANA FLOWER; AMINOMETHYLPROPANOL; INDIAN FRANKINCENSE; BUTYLENE GLYCOL; CALENDULA OFFICINALIS FLOWER; GREEN TEA LEAF; CAMPHOR (NATURAL); CARBOMER HOMOPOLYMER, UNSPECIFIED TYPE; FD&C BLUE NO. 1; FD&C YELLOW NO. 5; GLYCERIN; ILEX PARAGUARIENSIS LEAF; ISOPROPYL ALCOHOL; ISOPROPYL MYRISTATE; MELISSA OFFICINALIS LEAF; METHYL METHACRYLATE/GLYCOL DIMETHACRYLATE CROSSPOLYMER; .ALPHA.-TOCOPHEROL ACETATE; WATER

43473-095 4% Menthol PAIN RELIEF GEL

Active ingredient

Menthol 4%

Purpose

Pain Relief Gel

Uses

Temporarily relieves minor aches and pains of muscles and joints associated with: • simple backache • arthritis • strains • bruises • sprains

Warnings

For external use only.

Flammable:Keep away from excessive heat or open flame

When using this product • use only as directed • avoid contact with the eyes or on mucous membranes • do not apply to wounds or damaged skin • do not apply to irritated skin or if excessive irritation develops • do not bandage tightly or use with heating pad or device

Stop use and ask a doctor if • you experience pain, swelling or blistering of the skin • condition worsens, or if symptoms persist for more than 7 days or clear up and occur again within a few days • arthritic pain persists for more than 10 days, or redness is present, or in conditions affecting children under 12 years of age

If pregnant or breast-feeding, ask a health professional before use.

Keep out of reach of children.If swallowed, get medical help or contact a Poison Control Center right away.

Directions

• adults and children 12 years of age and older: rub a thin film over affected area not more than3 to 4 times daily • children under 12 years of age: consult a physician • wash hands after use with cool water

Other information

Store at room temperature • Protect from direct sunlight.

Inactive ingredients

Aloe Barbadensis Leaf Juice, Arctium Lappa Extract, Arnica Montana Flower Extract, Aminomethyl Propanol, Boswellia Serrata Extract, Butylene Glycol, Calendula Officinalis Flower Extract, Camellia Sinensis Leaf Extract, Camphor, Carbomer, FD&C Blue NO.1, FD&C Yellow No.5, Glycerin, Ilex Paraguariensis Leaf Extract, Isopropyl Alcohol, Isopropyl Myristate, Melissa Officinalis Leaf Extract, Methyl Methacrylate Crosspolymer, Tocopheryl Acetate, Water.

COOLING MENTHOL FORMULA

✓ Soothes sore muscles
✓ Relieves back, neck & joint pain
✓ Fast-absorbing & non-greasy

Mfd for and Distributed by:
Universal Distribution Center LLC
330 Applegarth Road, Monroe Township, NJ 08831

www.universaldc.com

MADE IN CHINA